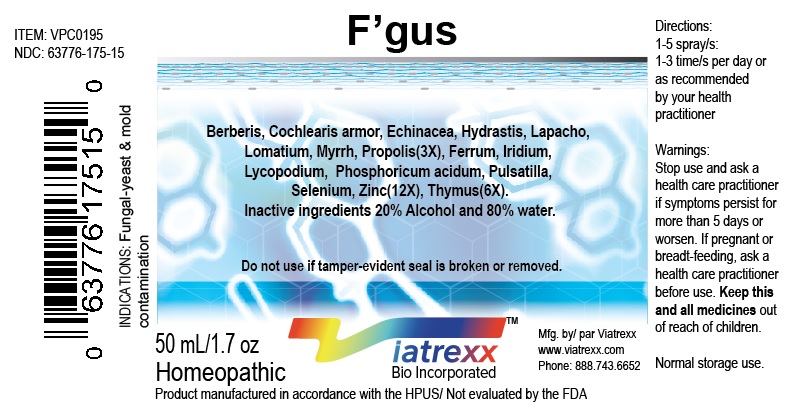 DRUG LABEL: Viatrexx-F gus
NDC: 63776-175 | Form: SPRAY
Manufacturer: VIATREXX BIO INCORPORATED
Category: homeopathic | Type: HUMAN OTC DRUG LABEL
Date: 20190319

ACTIVE INGREDIENTS: Echinacea Angustifolia 3 [hp_X]/1 mL; Goldenseal 3 [hp_X]/1 mL; Lycopodium Clavatum Spore 12 [hp_X]/1 mL; Selenium 12 [hp_X]/1 mL; Sus Scrofa Thymus 6 [hp_X]/1 mL; Bos Taurus Thymus 6 [hp_X]/1 mL; Zinc 12 [hp_X]/1 mL; Berberis Vulgaris Root Bark 3 [hp_X]/1 mL; Armoracia Rusticana Whole 3 [hp_X]/1 mL; Iron 12 [hp_X]/1 mL; Iridium 12 [hp_X]/1 mL; Handroanthus Impetiginosus Whole 3 [hp_X]/1 mL; Lomatium Dissectum Root 3 [hp_X]/1 mL; Myrrh 3 [hp_X]/1 mL; Phosphoric Acid 12 [hp_X]/1 mL; Propolis Wax 3 [hp_X]/1 mL; Anemone Pulsatilla 12 [hp_X]/1 mL
INACTIVE INGREDIENTS: Alcohol; Water

F gus

Active Ingredients

Acidum phosphoricum (12X), berberis 3X, Cochlearia armor 3X, Echinacea (3X), ferrum 12X, Hydrastis (3X), iridium 12X, Lapacho 3X, Lomatium 3X, Lycopodium (12X), Myrrh 3X, Propolis 3X, Pulsatilla 12X, Selenium 12X, Thymus (6X), Zinc (12X).

Description

Viatrexx-F gus is a homeopathic product composed of physiological (low dose and low low dose) natural micro nutrients. These micro particles are designed to nourish the system.

Uses

nutritional support for fungal, mold, bacteria challenges

Dosage

1-3 spray(s); 1-3 time(s) per day or as recommended by your health care practitioner.

Warnings

Stop use and ask a health care practitioner if symptoms persist for more than 5 days or worsen. If pregnant or breastfeeding, ask a health care practitioner before use.

Inactive Ingredients

20% Alcohol and 80% Water.

Product availability

Product may be acquired in 0.5, 30 ,50, 100, 250, 500, 1,000 mL bottles.

References upon request

To report SUSPECTED ADVERSE REACTIONS, contact the FDA at 1-800-FDA-1088 or www.fda.gov/medwatch

Distributed by
Viatrexx Bio Incorporated
Newark, DE, USA, 19713

Manufactured by
8046255 Canada Inc
Beloeil, Qc, J3G 6S3
Date of last revision March 2019

For Questions and comments
Info@Viatrexx.com
www.Viatrexx.com

PACKAGE LABEL.PRINCIPAL DISPLAY PANEL

NDC: 63776-175-11
Item: VPC0195
Viatrexx Bio Incorporated
Viatrexx-Fgus
0.5 mL ampule
For Oral and Topical Use
Expiry date: Lot #:
Manufactured for:
Viatrexx Bio Incorporated Newark, DE, USA, 19713
www.Viatrexx.com
Ingredients, homeopathic
See insert or www.viatrexx.com
Inactives: Alcohol 20%, Water 80%

NDC: 63776-175-14
Item: VPC0195
Viatrexx Bio Incorporated
Viatrexx-F gus 30 mL spray bottle
For Oral and Topical Use
Expiry date: Lot #:
Manufactured for:
Viatrexx Bio Incorporated Newark, DE, USA, 19713
www.Viatrexx.com
Ingredients, homeopathic
See insert or www.viatrexx.com
Inactives: Alcohol 20%, Water 80%

NDC: 63776-175-15
Item: VPC07195
Viatrexx Bio Incorporated
Viatrexx-F gus
50 mL spray bottle
For Oral and Topical Use
Expiry date: Lot #:
Manufactured for:
Viatrexx Bio Incorporated Newark, DE, USA, 19713
www.Viatrexx.com
Ingredients, homeopathic
See insert or www.viatrexx.com
Inactives: Alcohol 20%, Water 80%

NDC: 63776-175-16
Item: VPC0195
Viatrexx Bio Incorporated
Viatrexx-Fgus
100 mL bottle
For Oral and Topical Use
Expiry date: Lot #:
Manufactured for:
Viatrexx Bio Incorporated Newark, DE, USA, 19713
www.Viatrexx.com
Ingredients, homeopathic
See insert or www.viatrexx.com
Inactives: Alcohol 20%, Water 80%

NDC: 63776-175-17
Item: VPC0195
Viatrexx Bio Incorporated
Viatrexx-Fgus
250 mL bottle
For Oral and Topical Use
Expiry date: Lot #:
Manufactured for:
Viatrexx Bio Incorporated Newark, DE, USA, 19713
www.Viatrexx.com
Ingredients, homeopathic
See insert or www.viatrexx.com
Inactives: Alcohol 20%, Water 80%